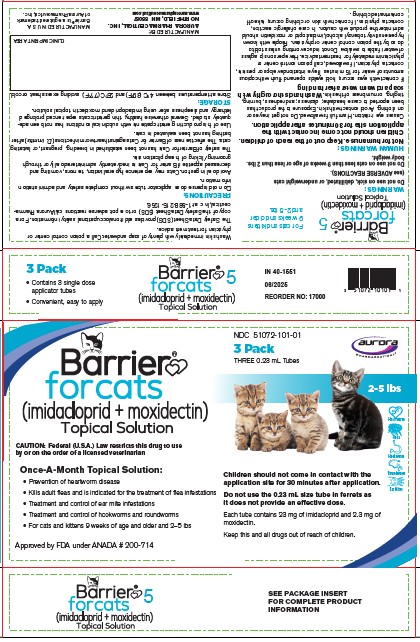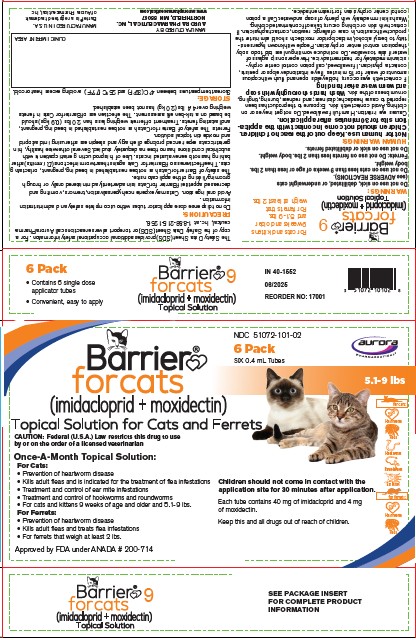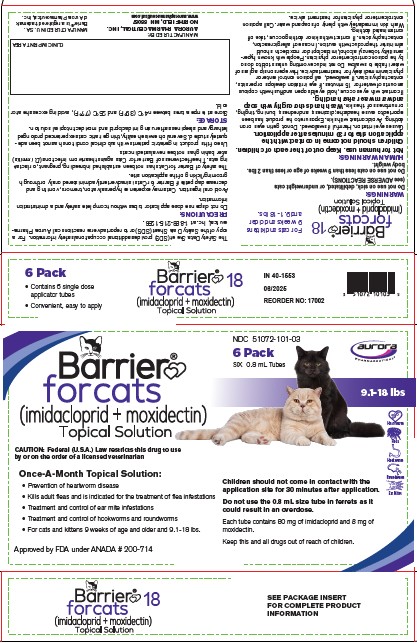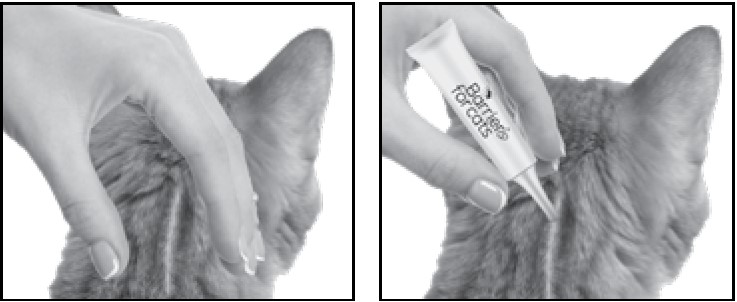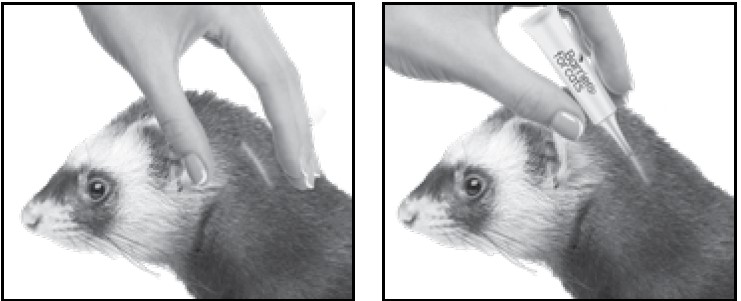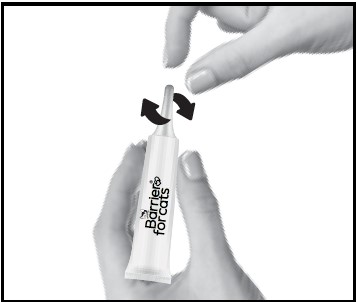 DRUG LABEL: BARRIER FOR CATS
NDC: 51072-101 | Form: SOLUTION
Manufacturer: Aurora Pharmaceutical, Inc
Category: animal | Type: PRESCRIPTION ANIMAL DRUG LABEL
Date: 20251211

ACTIVE INGREDIENTS: IMIDACLOPRID 100 mg/1 mL; MOXIDECTIN 10 mg/1 mL

Barrier® for Cats
(imidacloprid+moxidectin)
Topical Solution

Once-a-month topical solution for cats for the prevention of heartworm disease, kills adult fleas, is indicated for the treatment of flea infestations, as well as the treatment and control of ear mite infestations and intestinal parasite infections in cats and kittens 9 weeks of age and older and that weigh at least 2 lbs.

Once-a-month topical solution for ferrets for the prevention of heartworm disease, kills adult fleas, and is indicated for the treatment of flea infestations. Indicated for ferrets that weigh at least 2 lbs.

CAUTION:

Federal (U.S.A.) Law restricts this drug to use by or on the order of a licensed veterinarian.

DESCRIPTION:

Barrier for Cats (10 % imidacloprid + 1 % moxidectin) is a colorless to yellow ready-to-use solution packaged in single-dose applicator tubes for topical treatment of cats. The formulation and dosage schedule are designed to provide a minimum of 4.5 mg/lb (10.0 mg/kg) imidacloprid and 0.45 mg/lb (1.0 mg/kg) moxidectin based on body weight. Imidacloprid is a chloronicotinyl nitroguanidine insecticide. The chemical name of imidacloprid is 1-[(6-Chloro-3-pyridinyl)methyl]-N-nitro-2-imidazolidinimine. Moxidectin is a semisynthetic macrocyclic lactone endectocide derived from the actinomycete Streptomycetes cyaneogriseus noncyanogenus. The chemical name of moxidectin is [6R, 23E, 25S(E)]-5-0-Demethyl-28-deoxy-25-(1,3-dimethyl-1-butenyl)-6,28-epoxy-23-(methoxyimino) milbemycin B.

INDICATIONS:

Barrier for Cats is indicated for the prevention of heartworm disease caused by Dirofilaria immitis. Barrier for Cats kills adult fleas (Ctenocephalides felis) and is indicated for the treatment of flea infestations. Barrier for Cats is also indicated for the treatment and control of ear mite (Otodectes cynotis) infestations and the following intestinal parasites:

Intestinal Parasite |  | Intestinal Stage
Intestinal Parasite |  | Adult | Immature Adult | Fourth Stage Larvae
Hookworm Species | Ancylostoma tubaeforme | X | X | X
Roundworm Species | Toxocara cati | X |  | X

WARNINGS:

Do not use on sick, debilitated, or underweight cats (See ADVERSE REACTIONS). Do not use on cats less than 9 weeks of age or less than 2 lbs. body weight.

HUMAN WARNINGS:

Not for human use. Keep out of the reach of children.

Children should not come in contact with the application site for 30 minutes after application.

Causes eye irritation. Harmful if swallowed. Do not get in eyes or on clothing. Avoid contact with skin. Exposure to the product has been reported to cause headache; dizziness; and redness, burning, tingling, or numbness of the skin.

Wash hands thoroughly with soap and warm water after handling.

If contact with eyes occurs, hold eyelids open and flush with copious amounts of water for 15 minutes. If eye irritation develops or persists, contact a physician. If swallowed, call poison control center or physician immediately for treatment advice. Have person sip a glass of water if able to swallow. Do not induce vomiting unless told to do so by the poison control center or physician. People with known hypersensitivity to benzyl alcohol, imidacloprid or moxidectin should administer the product with caution. In case of allergic reaction, contact a physician. If contact with skin or clothing occurs, take off contaminated clothing. Wash skin immediately with plenty of soap and water. Call a poison control center or physician for treatment advice.

The Safety Data Sheet (SDS) provides additional occupational safety information. For a copy of the Safety Data Sheet (SDS), to report adverse reactions, or consumer questions call Aurora Pharmaceutical at 1-888-215-1256.

PRECAUTIONS:

Do not dispense dose applicator tubes without complete safety and administration information. Avoid oral ingestion. Cats may experience hypersalivation, tremors, vomiting and decreased appetite if Barrier for Cats is inadvertently administered orally or through grooming/licking of the application site. The safety of Barrier for Cats has not been established in breeding, pregnant, or lactating cats. The effectiveness of Barrier for Cats against heartworm infections (D. immitis) after bathing has not been evaluated in cats. Use of this product in geriatric patients with subclinical conditions has not been adequately studied. Several otherwise healthy, thin geriatric cats experienced prolonged lethargy and sleepiness after using this drug. (See ADVERSE REACTIONS.)

ADVERSE REACTIONS:

Field Study:Following treatment with imidacloprid and moxidectin topical solution or an active control, cat owners reported the following post-treatment reactions:

OBSERVATION | Imidacloprid and Moxidectin Topical Solution n = 113 | Active Control n = 38
Lethargy (protracted sleeping, poorly responsive) | 3 cats* (2.7 %) | None observed
Behavioral changes (e.g., agitated, excessive grooming, hiding, pacing, spinning) | 9 cats (8.0 %) | 1 cat (2.6 %)
Discomfort (e.g., scratching, rubbing, head-shaking) | 5 cats (4.4 %) | None observed
Hypersalivation (within 1 hour after treatment) | 3 cats (2.7 %) | None observed
Polydipsia | 3 cats (2.7 %) | None observed
Coughing and gagging | 1 cat (0.9 %) | None observed
* These three cats were from the same household and included one 13-yr-old cat in good health, one 15-yr-old FIV positive cat in good health, and one 15-yr-old, underweight cat in fair health. Lethargy was noted for 24 to 36 hrs after the first treatment only; one cat was unsteady at 48 hrs. These cats were not on other medications.

During another field study, a 16-year-old cat with renal disease slept in the same place without moving for two days following application. (See PRECAUTIONS.)

Laboratory Effectiveness Studies: Imidacloprid and moxidectin topicl solution was administered at the recommended dose to 215 cats in 20 effectiveness studies. One random-sourced cat exhibited signs consistent with either moxidectin toxicity or viral respiratory disease and died 26 hours after product application; necropsy findings were inconclusive as to the cause of death. A second cat that became ill 3 days after application of imidacloprid and moxidectin topical solution responded to treatment for respiratory infection and completed the study. A third cat became ill on day 3 and died with signs and lesions attributable to panleukopenia on day 7 after moxidectin application.

Post-Approval Experience: The following adverse events are based on post-approval adverse drug experience reporting. Not all adverse reactions are reported to FDA CVM. It is not always possible to reliably estimate the adverse event frequency or establish a causal relationship to product exposure using this data. The following adverse events in cats are listed in decreasing order of reporting frequency: hypersalivation, depression/lethargy, application site reactions (alopecia, pruritus, lesions, and erythema), decreased appetite, vomiting, hyperactivity, ataxia, trembling, and behavior disorder (hiding).

In some cases death has been reported.

In humans, ocular and dermal irritation, nausea, numbness or tingling of the mouth and lips, anaphylaxis, pruritus, vomiting, and tongue/taste abnormalities have been reported following exposure to this product.

To report suspected adverse events, for technical assistance or to obtain a copy of the Safety Data Sheet, contact Aurora Pharmaceutical at 1-888-215-1256 or www.aurorapharmaceutical.com.

For additional information about adverse drug experience reporting for animal drugs, contact FDA at 1-888-FDA-VETS or http://www.fda.gov/reportanimalae.

DOSAGE AND ADMINISTRATION:

The recommended minimum dose is 4.5 mg/lb (10.0 mg/kg) imidacloprid and 0.45 mg/lb (1.0 mg/kg) moxidectin, once a month, by topical administration.

Do not apply to irritated skin.

1. Remove one dose applicator tube from the package. As specified in the following table, administer the entire contents of the Barrier for Cats tube that correctly corresponds with the body weight of the cat.

Cat (lbs.) | Volume (mL) | Imidacloprid (mg) | Moxidectin (mg)
2–5 | 0.23 | 23 | 2.3
5.1–9 | 0.4 | 40 | 4
9.1–18* | 0.8 | 80 | 8
* Cats over 18 lbs. should be treated with the appropriate combination of Barrier for Cats tubes.

2. While holding the tube in an upright position, twist the cap to break the seal and then apply. The cap will remain on the tube.3.Part the hair on the back of the cat’s neck at the base of the head, until the skin is visible. Place the tip of the tube on the skin and apply the entire contents directly on the exposed skin. Lift tube away from skin before releasing pressure on tube.

3. Part the hair on the back of the cat’s neck at the base of the head, until the skin is visible. Place the tip of the tube on the skin and apply the entire contents directly on the exposed skin. Lift tube away from skin before releasing pressure on tube.

Do not get this product in the cat's mouth or eyes or allow the cat to lick the application site for 30 minutes. Treatment at the base of the head will minimize the opportunity for ingestion by grooming. In households with multiple pets, keep animals separated to prevent licking of the application site.

Stiff, matted hair or a damp, oily appearance of the hair may be observed at the application site on some cats. This is temporary and does not affect the safety and effectiveness of the product.

Heartworm Prevention: For prevention of heartworm disease, Barrier for Cats should be administered at one-month intervals. Barrier for Cats may be administered year-around or at a minimum should start one month before the first expected exposure to mosquitoes and should continue at monthly intervals until one month after the last exposure to mosquitoes. If a dose is missed and a 30-day interval between doses is exceeded, administer Barrier for Cats immediately and resume the monthly dosing schedule. When replacing another heartworm preventative product in a heartworm prevention program, the first treatment with Barrier for Cats should be given within one month of the last dose of the former medication. At the discretion of the veterinarian, cats older than 6 months of age may be tested to determine the presence of existing heartworm infection before treatment with Barrier for Cats (See ADVERSE REACTIONS – Post-Approval Experience).

Flea Treatment: For the treatment of flea infestations, Barrier for Cats should be administered at one-month intervals. If the cat is already infested with fleas when the first dose of Barrier for Cats is administered, adult fleas on the cat will be killed. However, re-infestation from the emergence of pre-existing pupae in the environment may continue to occur for six weeks or longer after treatment is initiated. Cats treated with imidacloprid, including those with pre-existing flea allergy dermatitis have shown clinical improvement as a direct result of elimination of fleas from the cat.

Ear Mite Treatment: For the treatment of ear mites (Otodectes cynotis), Barrier for Cats should be administered once as a single topical dose. Monthly use of Barrier for Cats will control any subsequent ear mite infestations.

Intestinal Nematode Treatment: For the treatment and control of intestinal hookworm infections caused by Ancylostoma tubaeforme (adults, immature adults and fourth stage larvae) and roundworm infections caused by Toxocara cati (adults and fourth stage larvae), Barrier for Cats should be administered once as a single topical dose.

ANIMAL SAFETY:

Studies in Kittens: Imidacloprid and moxidectin topical solution was topically applied at 0, 1, 3, and 5X the maximum dose to 48 healthy 9-week-old kittens on days 0, 28, and 56. Lethargy was observed in 1 kitten from the 3X group and 1 from the 5X group on the day after initial treatment; the kitten from the 3X group was also disoriented and ataxic. One kitten from the 3X group had a slow pupillary light response two days after treatment and one had tremors the day after treatment. Hypersalivation was seen in one kitten from the 5X group approximately six hours post-treatment. One kitten from the 3X group was scratching at the treatment site 2 days after treatment. Slight cough was noted in 7 different kittens (2-0X, 2-1X, and 3-5X) during the 13-day period following the first treatment. Histopathology showed granulomatous inflammation at the treatment site in three 1X kittens. Causal relationship to the drug could not be determined. Pulmonary inflammation (1-5X) and lymphoid hyperplasia (2-1X, 4-3X) were seen in treated kittens. In a second study, imidacloprid and moxidectin topical solution was topically applied at 0, 1.7, 5.2 and 8.7X the maximum dose to 48 healthy 9-week-old kittens every two weeks for 6 doses. One kitten in the 8.7X group apparently ingested an unknown amount of the drug and developed the following clinical signs prior to euthanasia: mydriasis, salivation, depression, vomiting, unsteadiness, rapid to slow to difficult breathing, poor pupillary response, generalized tremors, inability to move, and nystagmus. Two kittens in the 5.2X group developed mydriasis, salivation, depression, squinting, and poor appetite. A kitten in the 1.7X group developed mydriasis.

Dose Tolerance Study: Eight healthy juvenile cats were topically dosed with a single application of imidacloprid and moxidectin topical solution at 10 times the recommended dose volume. Mild, transient hypersalivation occurred in two of the cats.

Oral Study in Cats: The oral safety of imidacloprid and moxidectin topical solution was tested in case of accidental oral ingestion. The maximum topical dose was orally administered to twelve healthy 9-week-old kittens. Hypersalivation (8 of 12 kittens) and vomiting (12 of 12 kittens) were observed immediately post-treatment. Tremors developed in one kitten within 1 hour, resolving without treatment within the next hour. All 12 kittens were either anorexic or had decreased appetite for at least 1 day following treatment. In 3 kittens, the anorexia or decreased appetite continued into the second week following treatment. There was a post-treatment loss of body weight in treated kittens compared to control kittens. In a pilot safety study using kittens younger in age and lighter in weight than allowed by product labeling, an 8-week old kitten weighing 0.6 kg orally received 2X of the label topical dose (0.46 mL/kg). Immediately after dosing, it vomited, had labored breathing and slight tremors. Within 4 hours, it was normal, but was found dead on day 6. Necropsy could not determine the cause of death.

Study in Heartworm Positive Cats: Young adult cats were inoculated subcutaneously with third-stage D. immitis larvae. At 243–245 days post-infection, immunoserology and echocardiography were performed to identify cats with adult heartworm burdens similar to naturally-acquired infections. Two groups were treated topically with either imidacloprid and moxidectin topical solution at the label dose or placebo, once every 28 days, for three consecutive treatments. A third group was treated topically, once, with imidacloprid and moxidectin topical solution at 5X the label dose. Sporadic vomiting and labored breathing related to heartworm burden were observed in the treatment and control groups. There was no difference between treatment groups in the numbers of adult D. immitis recovered at study conclusion. No adverse reactions were associated with the topical application of imidacloprid and moxidectin topical solution to experimentally heartworm-infected cats.

FERRETS

Use only the 0.4 mL Barrier for Cats in ferrets. The 0.23 mL size does not provide an effective dose and the 0.8mL size could result in an overdose.

INDICATIONS:

For ferrets:

Barrier for Cats is indicated for the prevention of heartworm disease in ferrets caused by Dirofilaria immitis. Barrier for Cats kills adult fleas (Ctenocephalides felis) and is indicated for the treatment of flea infestations on ferrets.

WARNINGS:

Do not use on sick or debilitated ferrets.

PRECAUTIONS:

Do not dispense dose applicator tubes without complete safety and administration information.

The safety of Barrier for Cats has not been established in breeding, pregnant, and lactating ferrets.

Treatment of ferrets weighing less than 2.0 lbs (0.9 kg) should be based on a risk-benefit assessment.

The effectiveness of Barrier for Cats in ferrets weighing over 4.4 lbs (2.0 kg) has not been established.

ADVERSE REACTIONS:

Field Safety Study in Ferrets: Imidacloprid and moxidectin topical solution was topically administered to 131 client-owned ferrets at the recommended dose volume (0.4 mL). The ferrets ranged in age from 3 months to 7 years, and weighed between 0.5 and 1.86 kg (1.1 to 4.1 lbs). The dose of imidacloprid ranged between 21.5 to 80.2 mg/kg in this study. The dose of moxidectin ranged between 2.2 to 8.0 mg/kg in this study. Adverse reactions in ferrets following treatment included: pruritus/scratching, scabbing, redness, wounds and inflammation at the treatment site; lethargy; and chemical odor. These adverse reactions resolved without additional therapy. Owners also reported stiffening of the hair at the treatment site, however, this is expected with application of a topical product and is not considered an adverse reaction. Three human adverse reactions were reported. An owner's finger became red following skin contact with the product. One owner reported a headache caused by the chemical odor of the product. One owner reported a tingling sensation of the lips after kissing the treatment site.

Foreign Market Experience: Because the following events were reported voluntarily during post-approval use of the product in foreign markets, it is not always possible to reliably establish a causal relationship to drug exposure. Adverse events reported in ferrets topically treated with 0.4 mL imidacloprid + moxidectin for cats included: malaise, vomiting, diarrhea, shaking, mydriasis, hypersalivation with abnormal neurologic signs, seizures, death, generalized hematoma of the body, and alopecia at the treatment site. Adverse reactions in humans included: burning, tingling, numbness, bad taste in the mouth, dizziness, and headache.

ANIMAL SAFETY:

Ferrets: Imidacloprid and moxidectin topical solution was topically applied at 5X the recommended dose volume to six healthy 9-month-old ferrets on Study Days 0, 14, 28, and 42. Because the weights of the ferrets in this study ranged from 2.0 to 4.0 lb (0.9 kg to 1.8 kg), ferrets received a range of dosages from 51.0 to 106.9 mg/lb (112 to 235 mg/kg) of imidacloprid and 5 to 10.5 mg/lb (11 to 23 mg/kg) of moxidectin. The following abnormal clinical signs were reported during the study: wet, matted, and/or greasy appearance to the hair, shaking of the head and/or body, rubbing of dose site on cage, and shedding. Slight increases in phosphorous, potassium, aspartate aminotransferase (AST), and glucose were seen during the study, however, no clinical signs related to these bloodwork changes were reported.

Oral Safety Study: Imidacloprid and moxidectin topical solution was orally administered at the recommended dose volume (0.4 mL) to eight healthy ferrets on Study Day 0. Ferrets were 78 to 101 days old (11.1 to 14.4 weeks) and weighed between 1.1 to 1.8 lb (0.5 to 0.8 kg) body weight on the day of dosing, resulting in doses ranges of 22.0–36.8 mg/lb (48.3–81.0 mg/kg) imidacloprid and 2.2–3.7 mg/lb (4.8–8.0 mg/kg) moxidectin. The following abnormal clinical signs were reported immediately following oral administration of imidacloprid and moxidectin topical solution: vomiting (one ferret) and ataxia (two ferrets). All abnormalities resolved without treatment or supportive care.

DOSAGE AND ADMINISTRATION:

For ferrets:

The recommended minimum dose for a ferret is 9 mg/lb (20 mg/kg) imidacloprid and 0.9 mg/lb (2 mg/kg) moxidectin, once a month, by topical administration.

Ferret (lbs.) | Barrier for Cats | Volume (mL) | Imidacloprid (mg) | Moxidectin (mg)
2.0–4.4 | Barrier for Cats 9 | 0.4 | 40 | 4

Only the 0.4 mL applicator tube volume (Barrier for Cats 9) should be used on ferrets.

Do not apply to irritated skin.

1. Remove one dose applicator tube from the package. Administer the entire contents of the Barrier for Cats tube (0.4 mL).

2. While holding the tube in an upright position, twist the cap to break the seal and then apply. The cap will remain on the tube.

3. Part the hair on the back of the ferret's neck at the base of the head, until the skin is visible. Place the tip of the tube on the skin and apply the entire contents directly on the exposed skin. Lift tube away from skin before releasing pressure on tube.

Do not get this product in the ferret's mouth or eyes or allow the ferret to lick the application site for 30 minutes. Treatment at the base of the head will minimize the opportunity for ingestion by grooming. In households with multiple pets, keep animals separated to prevent licking of the application site.

Stiff, matted hair or a damp, oily appearance of the hair may be observed at the application site on some ferrets. This is temporary and does not affect the safety or effectiveness of the product.

Heartworm Prevention: For prevention of heartworm disease, Barrier for Cats should be administered at one-month intervals. Barrier for Cats may be administered year-round or at a minimum should start one month before the first expected exposure to mosquitoes and should continue at monthly intervals until one month after the last exposure to mosquitoes. If a dose is missed and a 30-day interval between doses is exceeded, administer Barrier for Cats immediately and resume the monthly dosing schedule.

Flea Treatment: For the treatment of flea infestations on ferrets, Barrier for Cats should be administered at one-month intervals. If the ferret is already infested with fleas when the first dose of Barrier for Cats is administered, adult fleas on the ferret will be killed. However, re-infestation from the emergence of pre-existing pupae in the environment may continue to occur for six weeks or longer after treatment is initiated.

STORAGE INFORMATION:

Store at temperatures between 4°C (39°F) and 25°C (77°F), avoiding excess heat or cold.

HOW SUPPLIED:

Applications Per Package 3 x 0.23 mL tubes 6 x 0.4 mL tubes 6 x 0.8 mL tubes May 2021 Approved by FDA under ANADA # 200-714 MANUFACTURED BY:
AURORA PHARMACEUTICAL, INC.
NORTHFIELD, MN 55057
www.aurorapharmaceutical.com MANUFACTURED IN U.S.A.
Barrier is a Trademark of Aurora Pharmaceutical, Inc.

Principal Display Panel - 0.23 mL Carton Label

2 – 5 lbs

Heartworm

Fleas

Hookworm

Roundworm

Ear Mites

3 Pack

Barrier® for cats

(imidacloprid+moxidectin)

Topical Solution

CAUTION: Federal (U.S.A.) Law restricts this drug to use by or on the order of a licensed veterinarian

Once-A-Month Topical Solution

- Prevention of heartworm disease
- Kills adult fleas and is indicated for the treatment of flea infestations
- Treatment and control of ear mite infestations
- Treatment and control of hookworms and roundworms
- For cats and kittens 9 weeks of age and older and 2 –5 lbs.

Children should not come in contact with the application site for 30 minutes after application.

Do not use the 0.23 mL size tube in ferrets as it does not provide an effective dose.

Each tube contains 23 mg of imidacloprid and 2.3 mg of moxidectin.

Keep this and all drugs out of reach of children.

Approved by FDA under ANADA # 200-714

THREE 0.23 mL Tubes

NDC 51072-101-01

IN 40-1551 06/2025

Principal Display Panel - 0.4 mL Carton Label

5.1 – 9 lbs

for
cats:

Heartworm

Fleas

Hookworm

Roundworm

Ear Mites

for
ferrets:

Heartworm

Fleas

6 Pack

Barrier® for cats

(imidacloprid+moxidectin)

Topical Solution for Cats and Ferrets

CAUTION: Federal (U.S.A.) Law restricts this drug to use by or on the order of a licensed veterinarian

Once-A-Month Topical Solution

For Cats:

- Prevention of heartworm disease
- Kills adult fleas and is indicated for the treatment of flea infestations
- Treatment and control of ear mite infestations
- Treatment and control of hookworms and roundworms
- For cats and kittens 9 weeks of age and olderand 5.1 – 9 lbs.

For Ferrets:

- Prevention of heartworm disease
- Kills adult fleas and treats flea infestations
- For ferrets that weigh at least 2 lbs.

Children should not come in contact with the application site for 30 minutes after application.

Each tube contains 40 mg of imidacloprid and 4 mg of moxidectin.

Keep this and all drugs out of reach of children.

Approved by FDA under ANADA # 200-714

SIX 0.4 mL Tube

NDC 51072-101-02

IN 40-1552 06/2025

Principal Display Panel - 0.8 mL Carton Label

9.1 - 18 lbs

Heartworm

Fleas

Hookworm

Roundworm

Ear Mites

6 Pack

Barrier® for cats

(imidacloprid+moxidectin)

Topical Solution

CAUTION: Federal (U.S.A.) Law restricts this drug to use by or on the order of a licensed veterinarian

Once-A-Month Topical Solution

- Prevention of heartworm disease
- Kills adult fleas and is indicated for the treatment of flea infestations
- Treatment and control of ear mite infestations
- Treatment and control of hookworms and roundworms
- For cats and kittens 9 weeks of age and older and 9.1 –18 lbs.

Children should not come in contact with the application site for 30 minutes after application.

Do not use the 0.8 mL size tube in ferrets as it could result in an overdose.

Each tube contains 80 mg of imidacloprid and 8 mg of moxidectin.

Keep this and all drugs out of reach of children.

Approved by FDA under ANADA # 200-714

SIX 0.8 mL Tubes

NDC 51072-101-03

IN 40-1553 06/2025